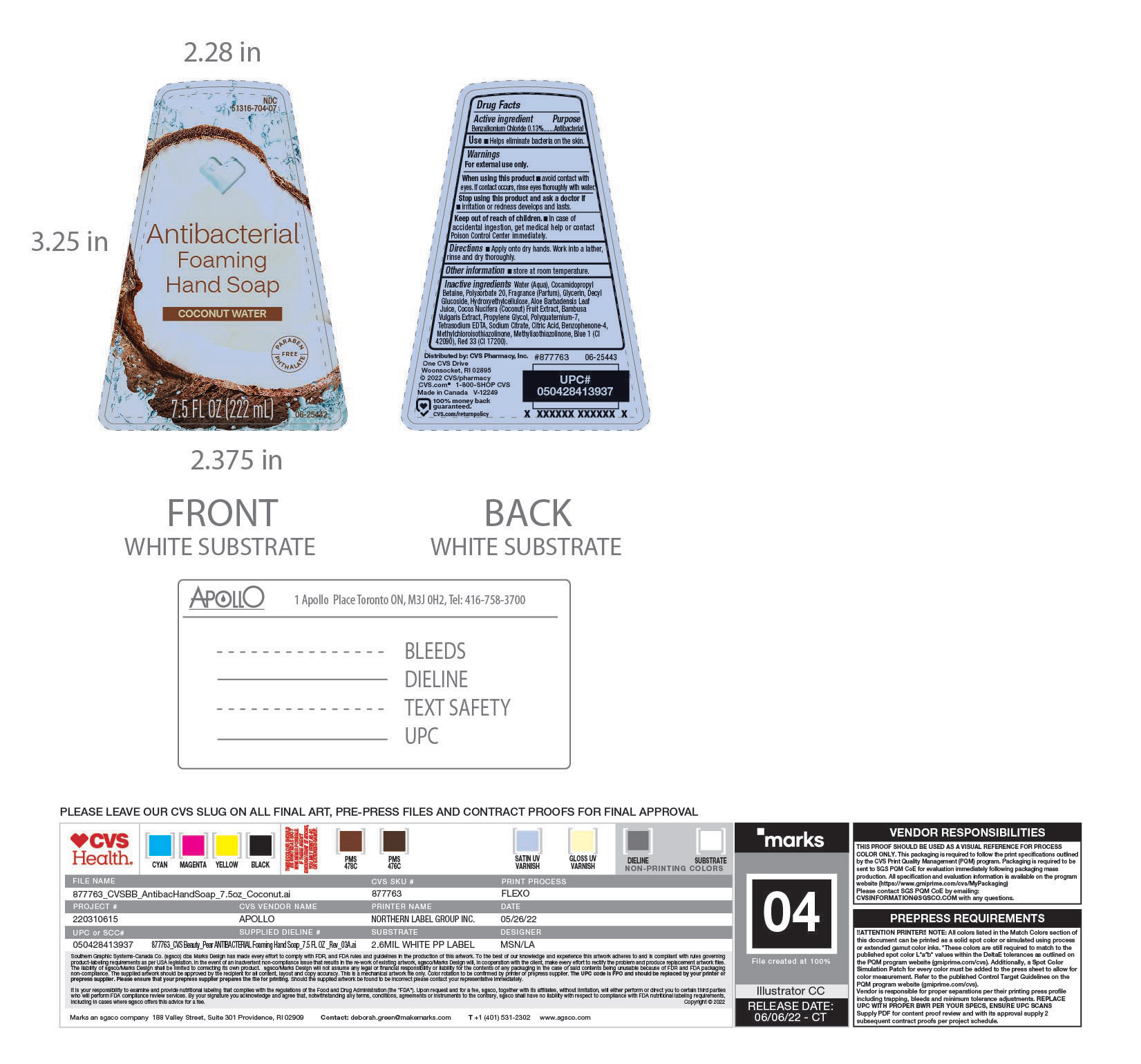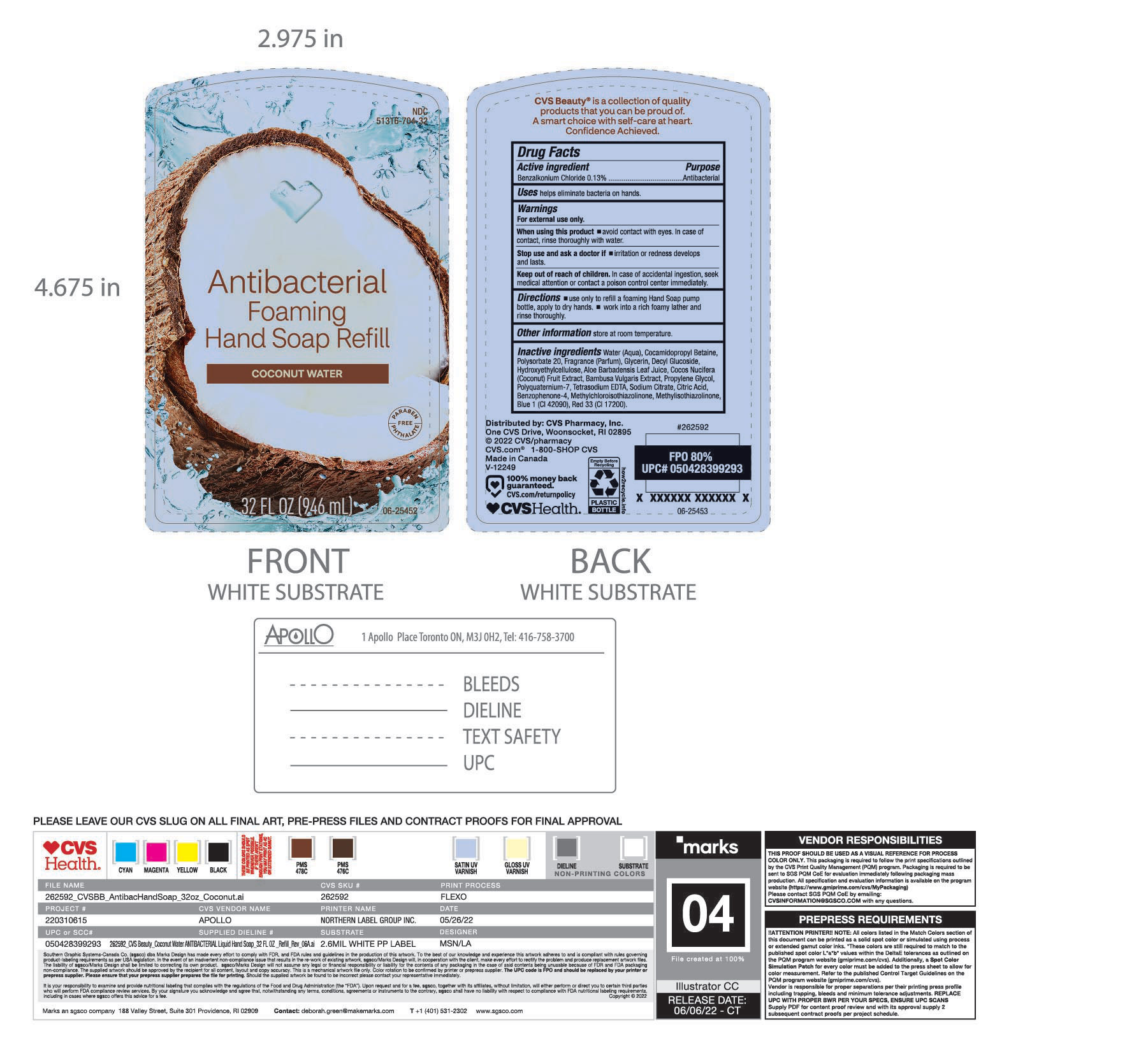 DRUG LABEL: CVS Pharmacy
NDC: 51316-704 | Form: SOAP
Manufacturer: CVS Pharmacy Inc
Category: otc | Type: HUMAN OTC DRUG LABEL
Date: 20250206

ACTIVE INGREDIENTS: BENZALKONIUM CHLORIDE 130 mg/100 mL
INACTIVE INGREDIENTS: DECYL GLUCOSIDE; HYDROXYETHYL CELLULOSE (2000 CPS AT 1%); EDETATE SODIUM; SODIUM CITRATE; SULISOBENZONE; POLYSORBATE 20; FRAGRANCE CLEAN ORC0600327; BAMBUSA VULGARIS LEAF; POLYQUATERNIUM-7; CITRIC ACID MONOHYDRATE; METHYLISOTHIAZOLINONE; D&C RED NO. 33; COCAMIDOPROPYL BETAINE; ALOE VERA LEAF; COCOS NUCIFERA (COCONUT) FRUIT; PROPYLENE GLYCOL; METHYLCHLOROISOTHIAZOLINONE; FD&C BLUE NO. 1; GLYCERIN; WATER

NDC 51316-704

ACTIVE INGREDIENT

Benzalkonium Chloride

PURPOSE

Hand washing

WARNINGS

For External Use Only

WHEN USING

Avoid contact with eyes. In case of contact, rinse throughly with water.

Ask a doctor if: Irritation or redness develops and lasts

KEEP OUT OF REACH OF CHILDREN

In case of accidental ingestion, seek medical attention or contact a poison control centre immediately.

DOSAGE AND ADMINISTRATION

Apply onto dry hands, work into a lather, rinse and dry throughly.

STORAGE AND HANDLING

Store at room temperature.

INACTIVE INGREDIENT

Water(Aqua), Cocamidopropyl Betaine, Polysorbate 20, Fragrance (Parfum), Glycerin, Decyl Glucoside, Hydroxyethylcellulose, Aloe Barbadensis, Leaf Juice, Cocos Nucifera (Coconut) Fruit Extract, Bambusa Vulgaris Extract, Propylene Glycol, Polyquaternium-7, Tetrasodium EDTA, Sodium Citrate, Citric Acid, Benzophenone -4, Methylcholoroisothiazolinone, Methylisothiazolinone, Blue 1 (Cl 42090), Red 33 (Cl 17200)

INDICATIONS AND USAGE

Helps eliminate bacteria on the skin